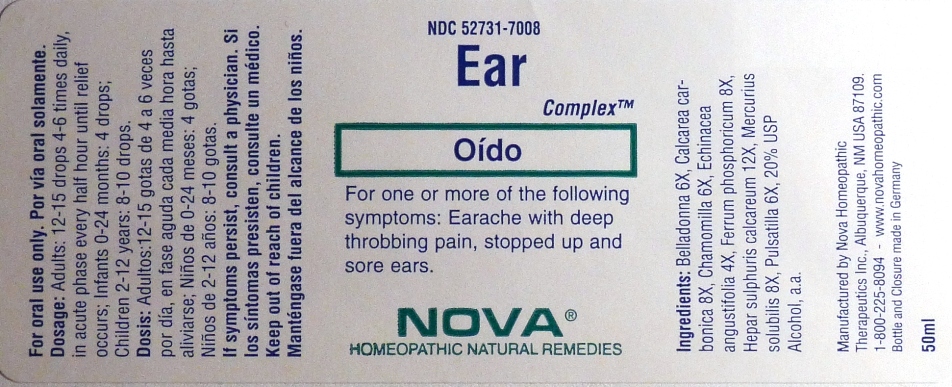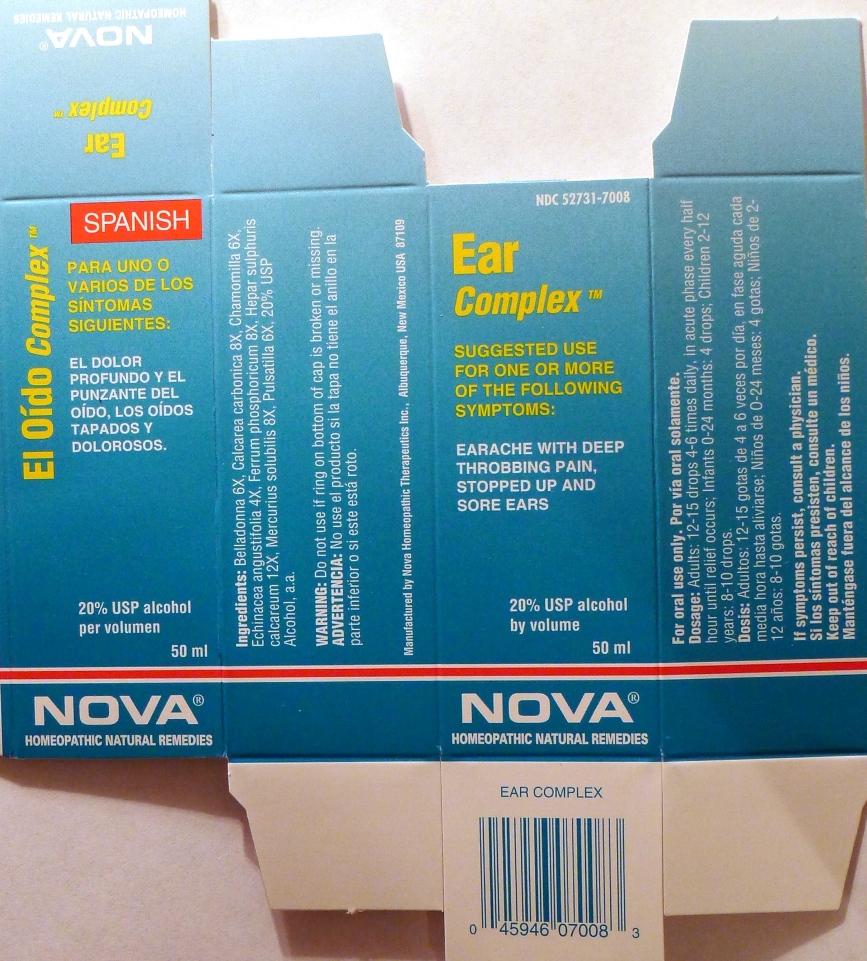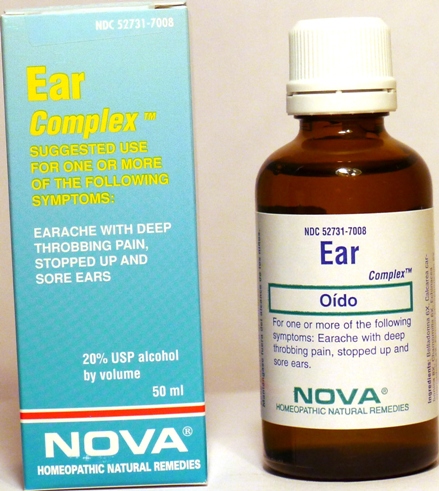 DRUG LABEL: Ear Complex
NDC: 52731-7008 | Form: LIQUID
Manufacturer: Nova Homeopathic Therapeutics, Inc.
Category: homeopathic | Type: HUMAN OTC DRUG LABEL
Date: 20110601

ACTIVE INGREDIENTS: ATROPA BELLADONNA 6 [hp_X]/1 mL; OYSTER SHELL CALCIUM CARBONATE, CRUDE 8 [hp_X]/1 mL; MATRICARIA RECUTITA 6 [hp_X]/1 mL; ECHINACEA ANGUSTIFOLIA 4 [hp_X]/1 mL; FERRUM PHOSPHORICUM 8 [hp_X]/1 mL; CALCIUM SULFIDE 8 [hp_X]/1 mL; MERCURIUS SOLUBILIS 12 [hp_X]/1 mL; PULSATILLA VULGARIS 6 [hp_X]/1 mL
INACTIVE INGREDIENTS: ALCOHOL

Ear Complex

Purpose:

Suggested use for one or more of the following symptoms:

Earache with deep throbbing pain,stopped up and sore ears

Usage and Dosage:

For oral use only.

DOSAGE AND ADMINISTRATION

Adults:
In Acute Phase:
12-15 drops, every half hour until relief occurs
When Relief Occurs:
12-15 drops, 4-6 times per day
Children 2-12 years:
8-10 drops, 4-6 times per day
Infants 0-24 months:
4 drops, 4-6 times per day

Warnings:

Keep out of reach of children.

WARNINGS

If symptoms persist, consult a physician.
Do not use if ring on bottom of cap is broken or missing.

Active Ingredients:

Belladonna 6X, Calcarea carbonica 8X, Chamomilla 6X, Echinacea angustifolia 4X, Ferrum phosphoricum 8X, Hepar sulphuris calcareum 12X, Mercurius solubilis 8X, Pulsatilla 6X

Inactive Ingredients:

Alcohol, 20% USP

QUESTIONS

Manufactured by Nova Homeopathic Therapeutics Inc., Albuquerque, New Mexico USA 87109
1-800-225-8094

PACKAGE LABEL

Ear Complex Product

Ear Complex Bottle Label

Ear Complex Box